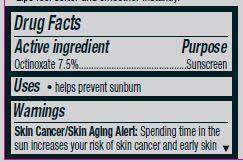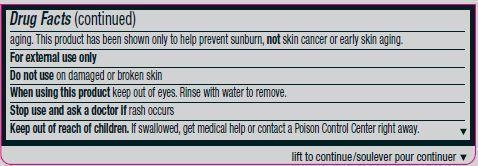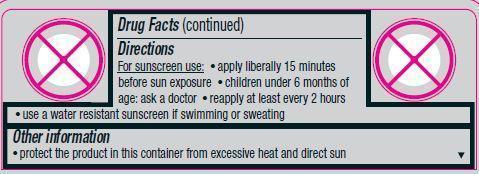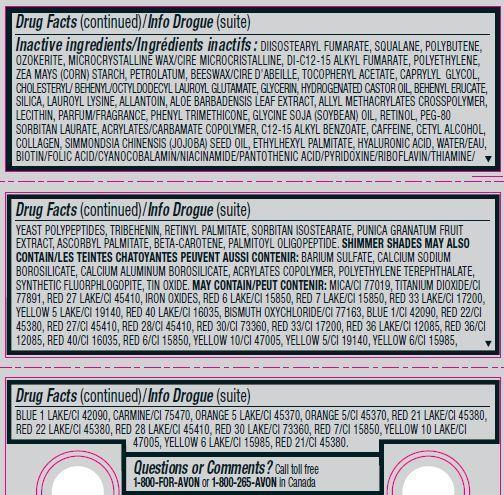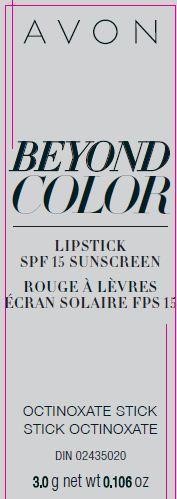 DRUG LABEL: Beyond Color
NDC: 10096-0329 | Form: LIPSTICK
Manufacturer: New Avon LLC
Category: otc | Type: HUMAN OTC DRUG LABEL
Date: 20190101

ACTIVE INGREDIENTS: OCTINOXATE 75 mg/1 g
INACTIVE INGREDIENTS: WATER

Beyond Color Lipstick SPF 15

Active ingredient
Octinoxate 7.5%................................

Purpose
...............................Sunscreen

Uses
• helps prevent sunburn

Warnings
Skin Cancer/Skin Aging Alert: Spending time in the sun increases your risk of skin cancer and early skin aging. This product has been shown only to help prevent sunburn, not skin cancer or early skin aging.
For external use only

Do not use on damaged or broken skin

When using this product keep out of eyes. Rinse with water to remove.

Stop use and ask a doctor if rash occurs

Keep out of reach of children. If swallowed, get medical help or contact a poison control center right away.

Directions

For sunscreen use:
• apply liberally 15 minutes before sun exposure
• children under 6 months of age: ask a doctor
• reapply at least every 2 hours
• use a water resistant sunscreen if swimming or sweating

Other information
• protect the product in this container from excessive heat and direct sun

INACTIVE INGREDIENT

Inactive ingredients: DIISOSTEARYL FUMARATE, SQUALANE, POLYBUTENE, OZOKERITE, MICROCRYSTALLINE WAX/CIRE MICROCRISTALLINE, DI-C12-15 ALKYL FUMARATE, POLYETHYLENE, ZEA MAYS (CORN) STARCH, PETROLATUM, BEESWAX/CIRE D’ABEILLE, TOCOPHERYL ACETATE, CAPRYLYL GLYCOL, CHOLESTERYL/ BEHENYL/OCTYLDODECYL LAUROYL GLUTAMATE, GLYCERIN, HYDROGENATED CASTOR OIL, BEHENYL ERUCATE, SILICA, LAUROYL LYSINE, ALLANTOIN, ALOE BARBADENSIS LEAF EXTRACT, ALLYL METHACRYLATES CROSSPOLYMER, LECITHIN, PARFUM/FRAGRANCE, PHENYL TRIMETHICONE, GLYCINE SOJA (SOYBEAN) OIL, RETINOL, PEG-80 SORBITAN LAURATE, ACRYLATES/CARBAMATE COPOLYMER, C12-15 ALKYL BENZOATE, CAFFEINE, CETYL ALCOHOL, COLLAGEN, SIMMONDSIA CHINENSIS (JOJOBA) SEED OIL, ETHYLHEXYL PALMITATE, HYALURONIC ACID, WATER/EAU, BIOTIN/FOLIC ACID/CYANOCOBALAMIN/NIACINAMIDE/PANTOTHENIC ACID/PYRIDOXINE/RIBOFLAVIN/THIAMINE/YEAST POLYPEPTIDES, TRIBEHENIN, RETINYL PALMITATE, SORBITAN ISOSTEARATE, PUNICA GRANATUM FRUIT EXTRACT, ASCORBYL PALMITATE, BETA-CAROTENE, PALMITOYL OLIGOPEPTIDE. SHIMMER SHADES MAY ALSO CONTAIN/LES TEINTES CHATOYANTES PEUVENT AUSSI CONTENIR: BARIUM SULFATE, CALCIUM SODIUM BOROSILICATE, CALCIUM ALUMINUM BOROSILICATE, ACRYLATES COPOLYMER, POLYETHYLENE TEREPHTHALATE, SYNTHETIC FLUORPHLOGOPITE, TIN OXIDE. MAY CONTAIN/PEUT CONTENIR: MICA/CI 77019, TITANIUM DIOXIDE/CI 77891, RED 27 LAKE/CI 45410, IRON OXIDES, RED 6 LAKE/CI 15850, RED 7 LAKE/CI 15850, RED 33 LAKE/CI 17200, YELLOW 5 LAKE/CI 19140, RED 40 LAKE/CI 16035, BISMUTH OXYCHLORIDE/CI 77163, BLUE 1/CI 42090, RED 22/CI 45380, RED 27/CI 45410, RED 28/CI 45410, RED 30/CI 73360, RED 33/CI 17200, RED 36 LAKE/CI 12085, RED 36/CI 12085, RED 40/CI 16035, RED 6/CI 15850, YELLOW 10/CI 47005, YELLOW 5/CI 19140, YELLOW 6/CI 15985, BLUE 1 LAKE/CI 42090, CARMINE/CI 75470, ORANGE 5 LAKE/CI 45370, ORANGE 5/CI 45370, RED 21 LAKE/CI 45380, RED 22 LAKE/CI 45380, RED 28 LAKE/CI 45410, RED 30 LAKE/CI 73360, RED 7/CI 15850, YELLOW 10 LAKE/CI 47005, YELLOW 6 LAKE/CI 15985, RED 21/CI 45380.

Questions or Comments?
Call toll free 1-800-FOR-AVON or 1-800-265-AVON
in Canada